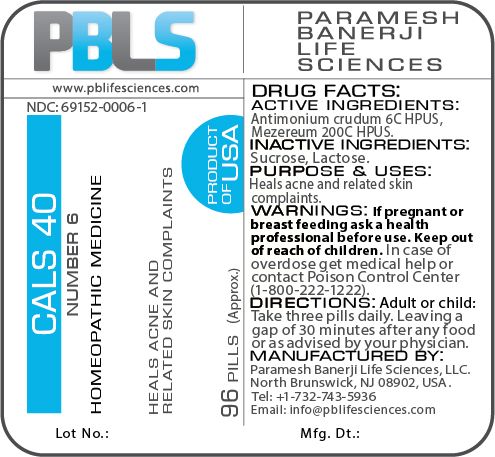 DRUG LABEL: Cals 40 (Number 6)
NDC: 69152-0006 | Form: PELLET
Manufacturer: Paramesh Banerji Life Sciences LLC
Category: homeopathic | Type: HUMAN OTC DRUG LABEL
Date: 20180205

ACTIVE INGREDIENTS: DAPHNE MEZEREUM BARK 200 [hp_C]/1 1; ANTIMONY TRISULFIDE 6 [hp_C]/1 1
INACTIVE INGREDIENTS: SUCROSE; LACTOSE

DRUG FACTS: Active Ingredients

Antimonium crudum 6C HPUS, Mezereum 200C HPUS

Inactive Ingredients

Sucrose, Lactose

Purpose

Heals acne and related skin complaints

Uses

Heals acne and related skin complaints

Warnings

If pregnant or breast feeding ask a health professional before use.

Keep out of reach of children. In case of overdose, get medical help or contact a Poison Control Center (1-800-222-1222) right away.

Direction

Adult or child: Take three pills daily. Leaving a gap of 30 minutes after any food or as advised by your physician.

Manufactured by

Paramesh Banerji Life Sciences, LLC.

North Brunswick, NJ 08902, USA.

Tel: +1-732-743-5936

Email: info@pblifesciences.com

Principal Display Panel

NDC: 69152-0006-1

Cals 40

Number 6

Homeopathic Medicine

Heals acne and related skin complaints

96 Pills (Approx.)

Product of USA